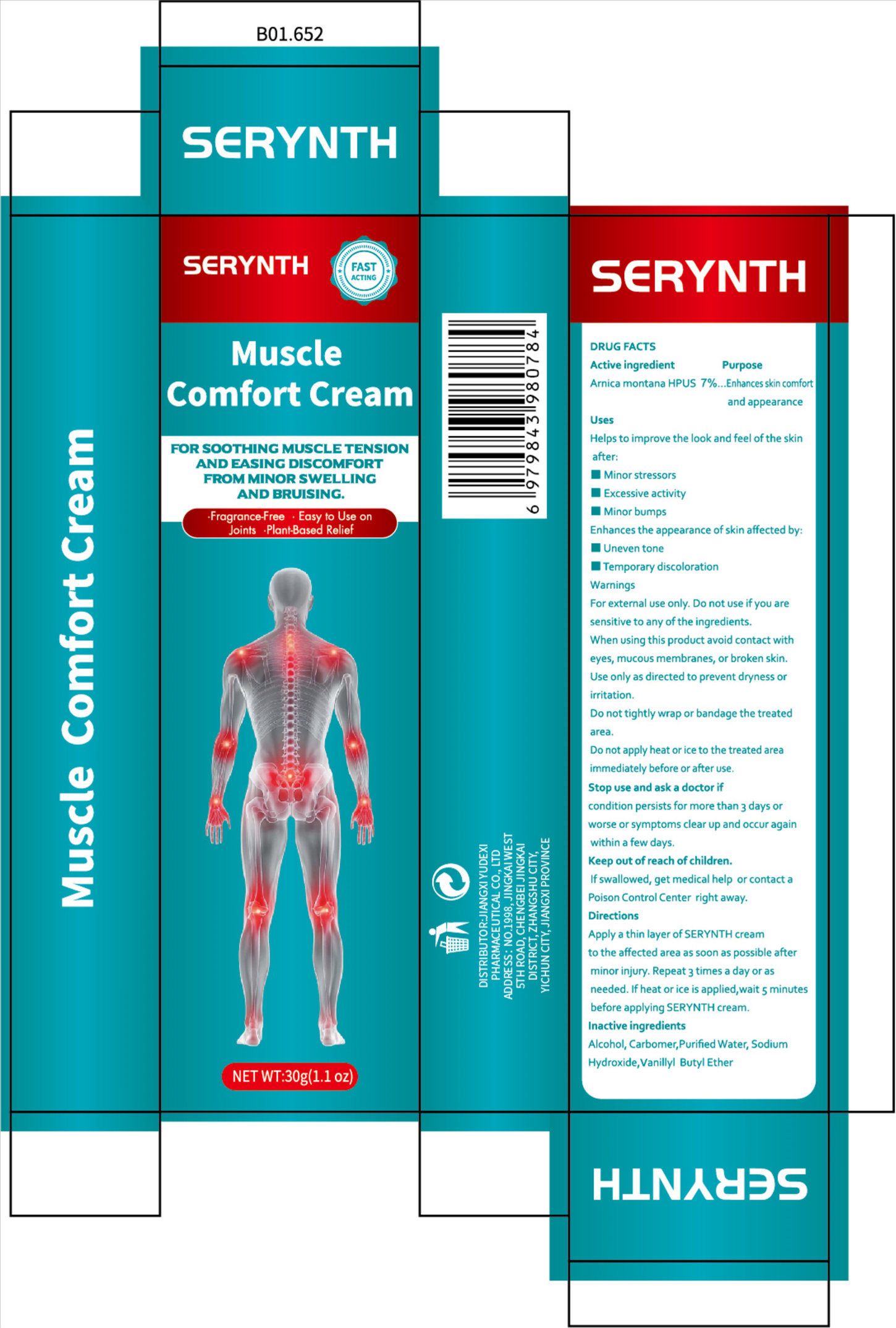 DRUG LABEL: SERYNTH Muscle Comfort
NDC: 85248-106 | Form: CREAM
Manufacturer: Jiangxi Yudexi Pharmaceutical Co., LTD
Category: otc | Type: HUMAN OTC DRUG LABEL
Date: 20260208

ACTIVE INGREDIENTS: ARNICA MONTANA 7 g/100 g
INACTIVE INGREDIENTS: WATER; VANILLYL BUTYL ETHER; SODIUM HYDROXIDE; ALCOHOL; CARBOMER

85248-106

Active Ingredient

Arnica montana HPUS7%

Purpose

Enhances skin comfor and appearance

Use

Helps to improve the look and feel ofthe skin
after: ■Minor stressors■Excessive activity ■ Minor bumps Enhances the appearance of skin affected by: ■ Uneven tone■Temporary discoloration

Warnings

For external use only

Do not use if you are sensitive to any of the ingredients.

When Using

When using this product avoid contact with eyes, mucous membranes, or broken skin.Use only as directed to prevent dryness or
irritation.
Do not tightly wrap or bandage the treated area. Do not apply heat or ice to the treated area immediately before or after use.

Stop Use

condition persists for more than 3 days or worse or symptoms clear up and occur again within a few days.

Ask Doctor

condition persists for more than 3 days or worse or symptoms clear up and occur again within a few days.

Keep Oot Of Reach Of Children

lf swallowed, get medical help or contact a Poison Control Center right away

Directions

Apply a thin layer of SERYNTH cream to the affected area as soon as possible after minor injury. Repeat 3 times a day or as needed. If heat or ice is applied,wait 5 minutes before applying SERYNTH cream,

Inactive ingredients

Alcohol, Carbomer,Purified Water, Sodium Hydroxide,Vanillyl Butyl Ether